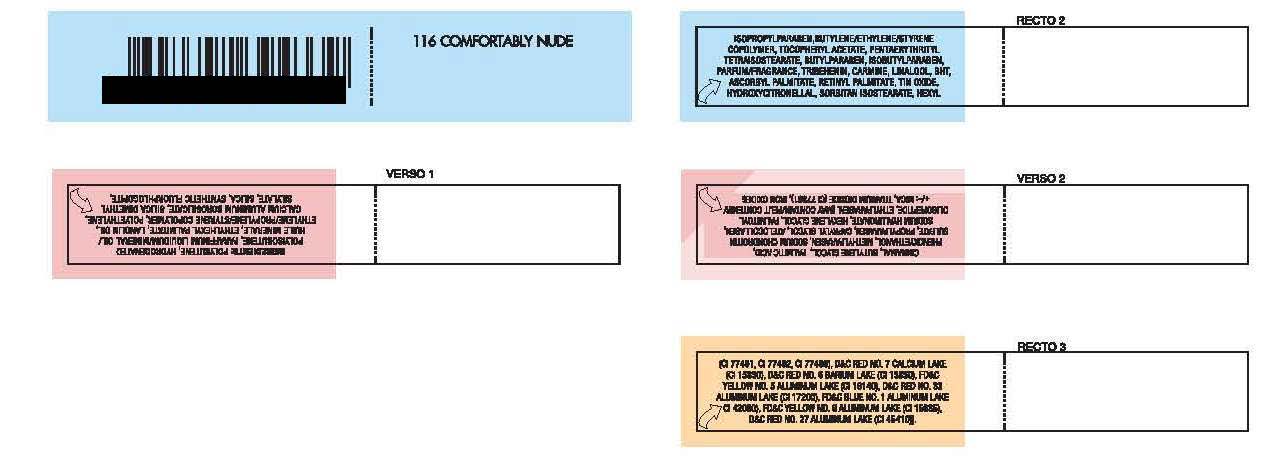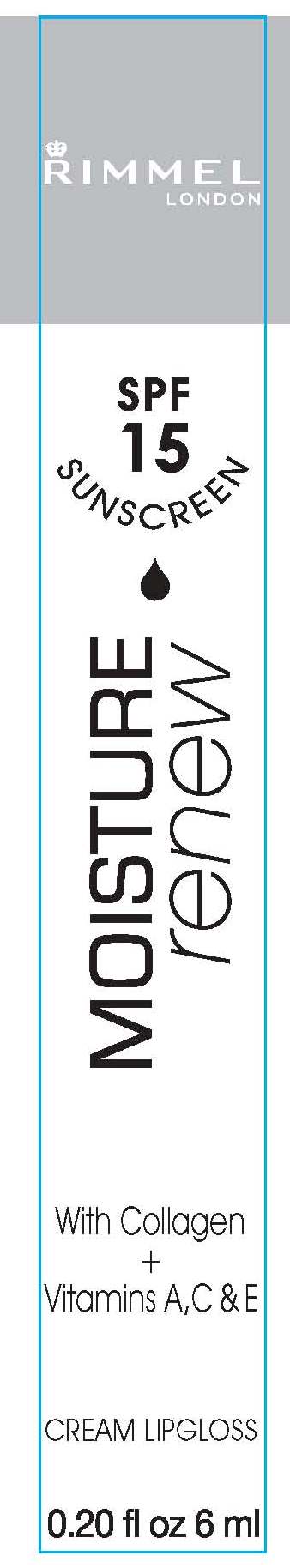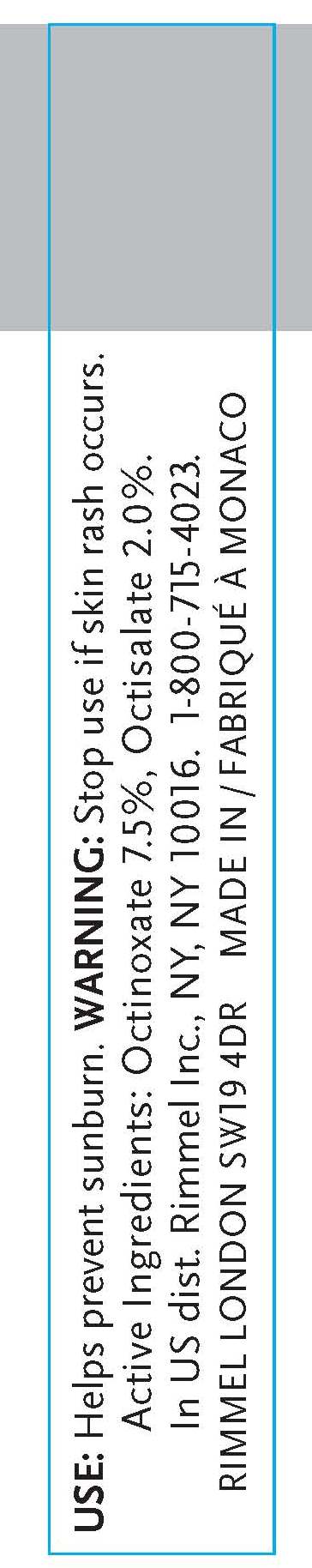 DRUG LABEL: Rimmel London
NDC: 59351-0331 | Form: CREAM
Manufacturer: Lancaster S.A.M.
Category: otc | Type: HUMAN OTC DRUG LABEL
Date: 20101020

ACTIVE INGREDIENTS: OCTINOXATE .012 mL/6 mL; OCTISALATE .12 mL/6 mL
INACTIVE INGREDIENTS: MINERAL OIL; ETHYLHEXYL PALMITATE; LANOLIN; ETHYLENE; ALUMINUM; SILICON DIOXIDE; ISOPROPYLPARABEN; ETHYLENE; .ALPHA.-TOCOPHEROL ACETATE, D-; BUTYLPARABEN; ISOBUTYLPARABEN; TRIBEHENIN; LINALOOL, (+/-)-; BUTYLATED HYDROXYTOLUENE; ASCORBYL PALMITATE; VITAMIN A PALMITATE; STANNIC OXIDE; HYDROXYCITRONELLAL; SORBITAN; .ALPHA.-HEXYLCINNAMALDEHYDE; BUTYLENE GLYCOL; PALMITIC ACID; PHENOXYETHANOL; METHYLPARABEN; SULFATE ION; PROPYLPARABEN; CAPRYLYL GLYCOL; HYALURONATE SODIUM; HEXYLENE GLYCOL; ETHYLPARABEN; MICA; TITANIUM DIOXIDE; IRON; CALCIUM; BARIUM

Rimmel London Moisture Renew Lipgloss Comfortably Nude (116) SPF 15 Sunscreen

INDICATIONS AND USAGE

USE: Helps prevent sunburn.

WARNINGS

WARNING: Stop use if skin rash occurs.

Active Ingredients: Octinoxate 7.5%, Octisalate 2.0%.

INACTIVE INGREDIENT

COSMETIC INGREDIENTS: POLYBUTENE, HYDROGENATED
POLYISOBUTENE, PARAFFINUM LIQUIDUM/MINERAL OIL/
HUILE MINERALE, ETHYLHEXYL PALMITATE, LANOLIN OIL,
ETHYLENE/PROPYLENE/STYRENE COPOLYMER, POLYETHYLENE,
CALCIUM ALUMINUM BOROSILICATE, SILICA DIMETHYL
SILYLATE, SILICA, SYNTHETIC FLUORPHLOGOPITE,
ISOPROPYLPARABEN,BUTYLENE/ETHYLENE/STYRENE
COPOLYMER, TOCOPHERYL ACETATE, PENTAERYTHRITYL
TETRAISOSTEARATE, BUTYLPARABEN, ISOBUTYLPARABEN,
PARFUM/FRAGRANCE, TRIBEHENIN, CARMINE, LINALOOL, BHT,
ASCORBYL PALMITATE, RETINYL PALMITATE, TIN OXIDE,
HYDROXYCITRONELLAL, SORBITAN ISOSTEARATE, HEXYL
CINNAMAL, BUTYLENE GLYCOL, PALMITIC ACID,
PHENOXYETHANOL, METHYLPARABEN, SODIUM CHONDROITIN
SULFATE, PROPYLPARABEN, CAPRYLYL GLYCOL, ATELOCOLLAGEN,
SODIUM HYALURONATE, HEXYLENE GLYCOL, PALMITOYL
OLIGOPEPTIDE, ETHYLPARABEN. [MAY CONTAIN/PEUT CONTENIR/
: MICA, TITANIUM DIOXIDE (CI 77891), IRON OXIDES
(CI 77491, CI 77492, CI 77499), DandC RED NO. 7 CALCIUM LAKE
(CI 15850), DandC RED NO. 6 BARIUM LAKE (CI 15850), FDandC
YELLOW NO. 5 ALUMINUM LAKE (CI 19140), DandC RED NO. 33
ALUMINUM LAKE (CI 17200), FDandC BLUE NO. 1 ALUMINUM LAKE
CI 42090), FDandC YELLOW NO. 6 ALUMINUM LAKE (CI 15985),
DandC RED NO. 27 ALUMINUM LAKE (CI 45410)].

PACKAGE LABEL

RIMMEL LONDON
SPF 15 SUNSCREEN
MOISTURE RENEW
WITH COLLAGEN AND VITAMINS A, C and E
CREAM LIPGLOSS
0.20 fl oz 6 ml